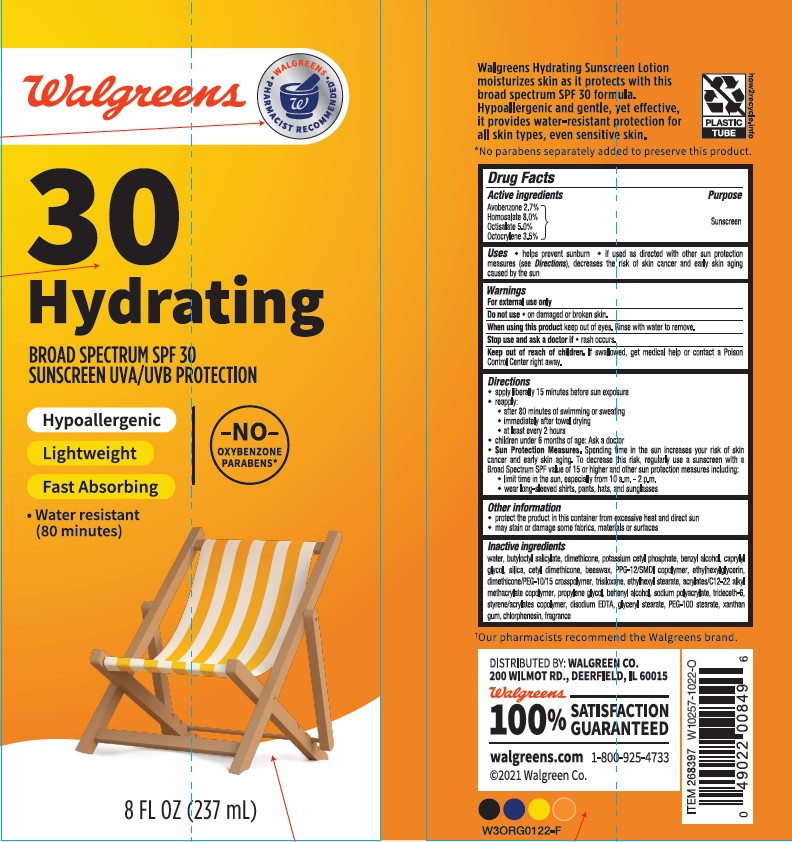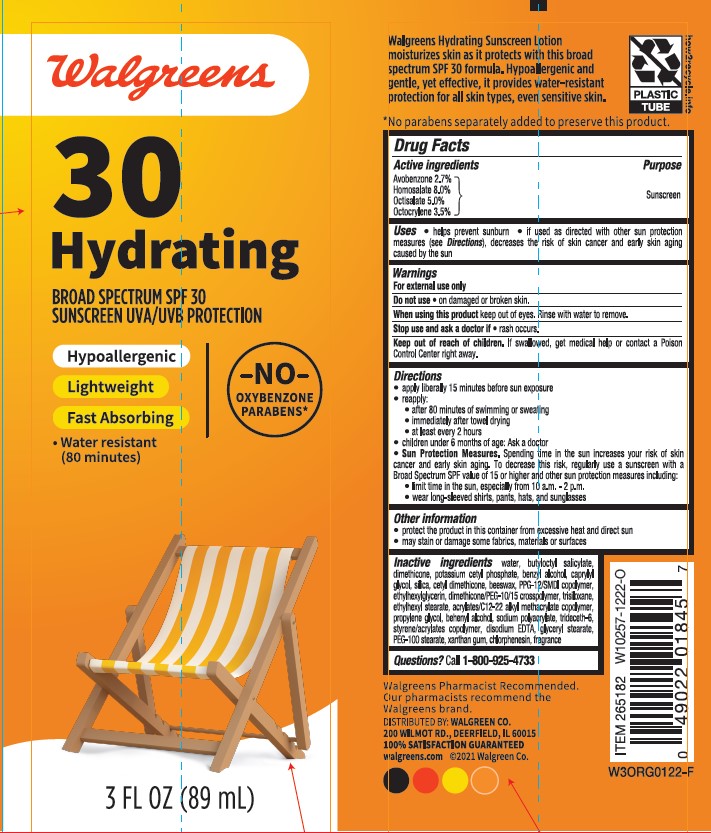 DRUG LABEL: Walgreens SPF 30 Hydrating
NDC: 0363-0146 | Form: LOTION
Manufacturer: WALGREEN COMPANY
Category: otc | Type: HUMAN OTC DRUG LABEL
Date: 20241011

ACTIVE INGREDIENTS: OCTOCRYLENE 35 mg/1 mL; OCTISALATE 50 mg/1 mL; HOMOSALATE 80 mg/1 mL; AVOBENZONE 27 mg/1 mL
INACTIVE INGREDIENTS: WATER; DIMETHICONE; POTASSIUM CETYL PHOSPHATE; BENZYL ALCOHOL; BUTYLOCTYL SALICYLATE; BUTYL ACRYLATE/C16-C20 ALKYL METHACRYLATE/METHACRYLIC ACID/METHYL METHACRYLATE COPOLYMER; CAPRYLYL GLYCOL; SILICON DIOXIDE; ETHYLHEXYLGLYCERIN; POLYETHYLENE GLYCOL 500; TRISILOXANE; DOCOSANOL; SODIUM POLYACRYLATE (8000 MW); CETYL DIMETHICONE 150; YELLOW WAX; PPG-12/SMDI COPOLYMER; POLYETHYLENE GLYCOL 700; ETHYLHEXYL STEARATE; TRIDECETH-6; PEG-100 STEARATE; XANTHAN GUM; BUTYL METHACRYLATE/METHYL METHACRYLATE/METHACRYLIC ACID/STYRENE CROSSPOLYMER; EDETATE DISODIUM ANHYDROUS; GLYCERYL MONOSTEARATE; CHLORPHENESIN

Walgreens SPF 30 Hydrating Lotion

Active ingredients

Avobenzone 2.7%, Homosalate 8.0%, Octisalate 5.0%, Octocrylene 3.5%

Purpose

Sunscreen

Uses

- helps prevent sunburn
- if used as directed with other sun protection measures (see Directions), decreases the risk of skin cancer and early skin aging caused by the sun

Warnings

For external use only

Do not use

on damaged or broken skin

When using this product

keep out of eyes. Rinse with water to remove.

Stop use and ask a doctor

if rash occurs.

Keep out of reach of children.

If product is swallowed, get medical help or contact a Poison Control Center right away.

Directions

• apply liberally 15 minutes before sun exposure
• reapply:
• after 80 minutes of swimming or sweating
• immediately after towel drying
• at least every 2 hours
• Sun Protection Measures. Spending time in the sun increases your risk of skin cancer and early skin aging. To decrease this risk, regularly use a sunscreen with a Broad Spectrum SPF value of 15 or higher and other sun protection measures including:
• limit time in the sun, especially from 10 a.m. - 2 p.m.
• wear long-sleeved shirts, pants, hats, and sunglasses
• children under 6 months: Ask a doctor

Other information

• protect the product on this container from excessive heat and direct sun
• may stain or damage some fabrics, materials or surfaces

Inactive ingredients

Water, Butyloctyl Salicylate, Dimethicone, Potassium Cetyl Phosphate, Benzyl Alcohol, Caprylyl Glycol, Silica, Cetyl Dimethicone, Beeswax, PPG-12/SMDI Copolymer, Ethylhexylglycerin, Dimethicone/PEG-10/15 Crosspolymer, Trilsiloxane, Ethylhexyl Stearate,Acrylates/C12-22 Alklmethacrylate Copolymer, Propylene Glycol, Behenyl Alcohol, Sodium Polyacrylate, Trideceth-6, Styrene/Acrylates Copolymer, Disodium EDTA, Glyceryl Stearate, PEG-100 Stearate, Xanthan Gum, Chlorphenesin, Fragrance.